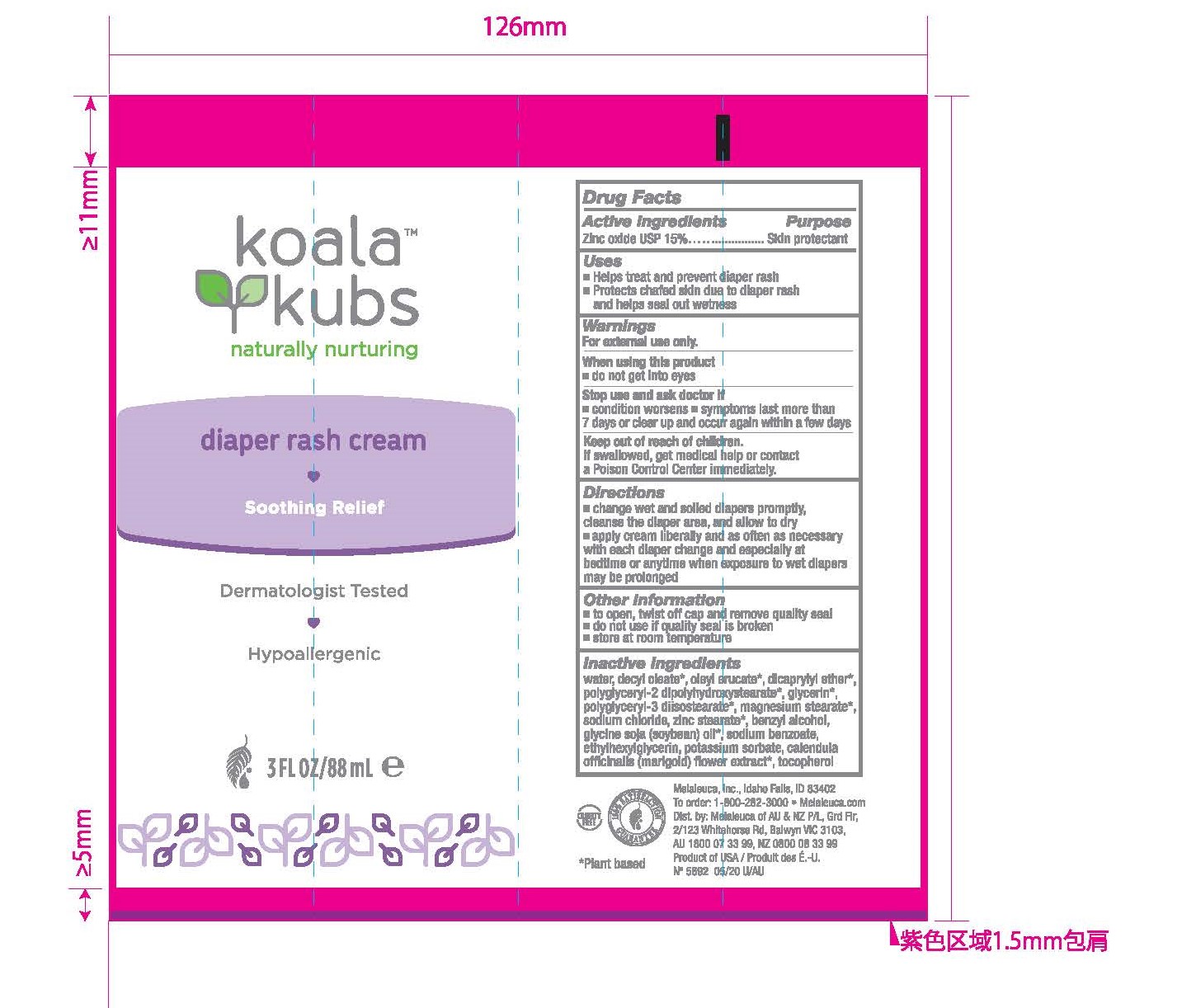 DRUG LABEL: Koala Kubs Diaper Rash Cream
NDC: 54473-333 | Form: CREAM
Manufacturer: Melaleuca, Inc.
Category: otc | Type: HUMAN OTC DRUG LABEL
Date: 20250320

ACTIVE INGREDIENTS: ZINC OXIDE 150 mg/88 mL
INACTIVE INGREDIENTS: ETHYLHEXYLGLYCERIN 0.154 mL/88 mL; POTASSIUM SORBATE 0.1408 mL/88 mL; CALENDULA OFFICINALIS FLOWER 0.011 mL/88 mL; WATER 44.4576 mL/88 mL; DECYL OLEATE 8.8 mL/88 mL; TOCOPHEROL 0.00132 mL/88 mL; POLYGLYCERYL-2 DIPOLYHYDROXYSTEARATE 2.64 mL/88 mL; SOYBEAN OIL 0.42856 mL/88 mL; ZINC STEARATE 0.88 mL/88 mL; OLEYL ERUCATE 4.4 mL/88 mL; SODIUM BENZOATE 0.2816 mL/88 mL; GLYCERIN 2.64 mL/88 mL; DICAPRYLYL ETHER 4.4 mL/88 mL; POLYGLYCERYL-3 DIISOSTEARATE 1.76 mL/88 mL; MAGNESIUM STEARATE 1.76 mL/88 mL; SODIUM CHLORIDE 1.32 mL/88 mL; BENZYL ALCOHOL 0.72512 mL/88 mL

Koala Kubs Diaper Rash Cream

Active Ingredients

Zinc Oxide USP 15%

Purpose

Skin Protectant

Uses

- Helps treat and prevent diaper rash
- Protects chaffed skin due to diaper rash and helps seal out wetness

When using this product

- do not get into eyes

Stop use and ask doctor if

- condition worsens
- symptoms last more than 7 days or clear up and occur again within a few days

Keep out of reach of children

If swallowed, get medical help or contact a Poison Control Center immediately.

Directions

- Change wet and soiled diapers promptly, cleanse the diaper area, and allow to dry
- Apply cream liberally and as often as necessary with each diaper change and especially at bedtime or anytime when exposure to wet diapers may be prolonged.

Other Information

- to open, twist off cap and remove quality seal
- do not use if quality seal is broken
- store at room temperature

Inactive Ingredients

Inactive Ingredients: water, decyl oleate, oleyl erucate, dicaprylyl ether, polyglyceryl-2 dipolyhydroxystearate, glycerin, polyglyceryl-3 diisostearate, magnesium stearate, sodium chloride, zinc stearate, benzyl alcohol, glycine soja (soybean) oil, sodium benzoate, ethylhexylglycerin, potassium sorbate, calendula officinalis (marigold) flower extract, tocopherol

Warnings

For external use only

Purpose

Skin Protectant

Uses

- Helps treat and prevent diaper rash
- Protects chafed skin due to diaper rash and helps seal out wetness